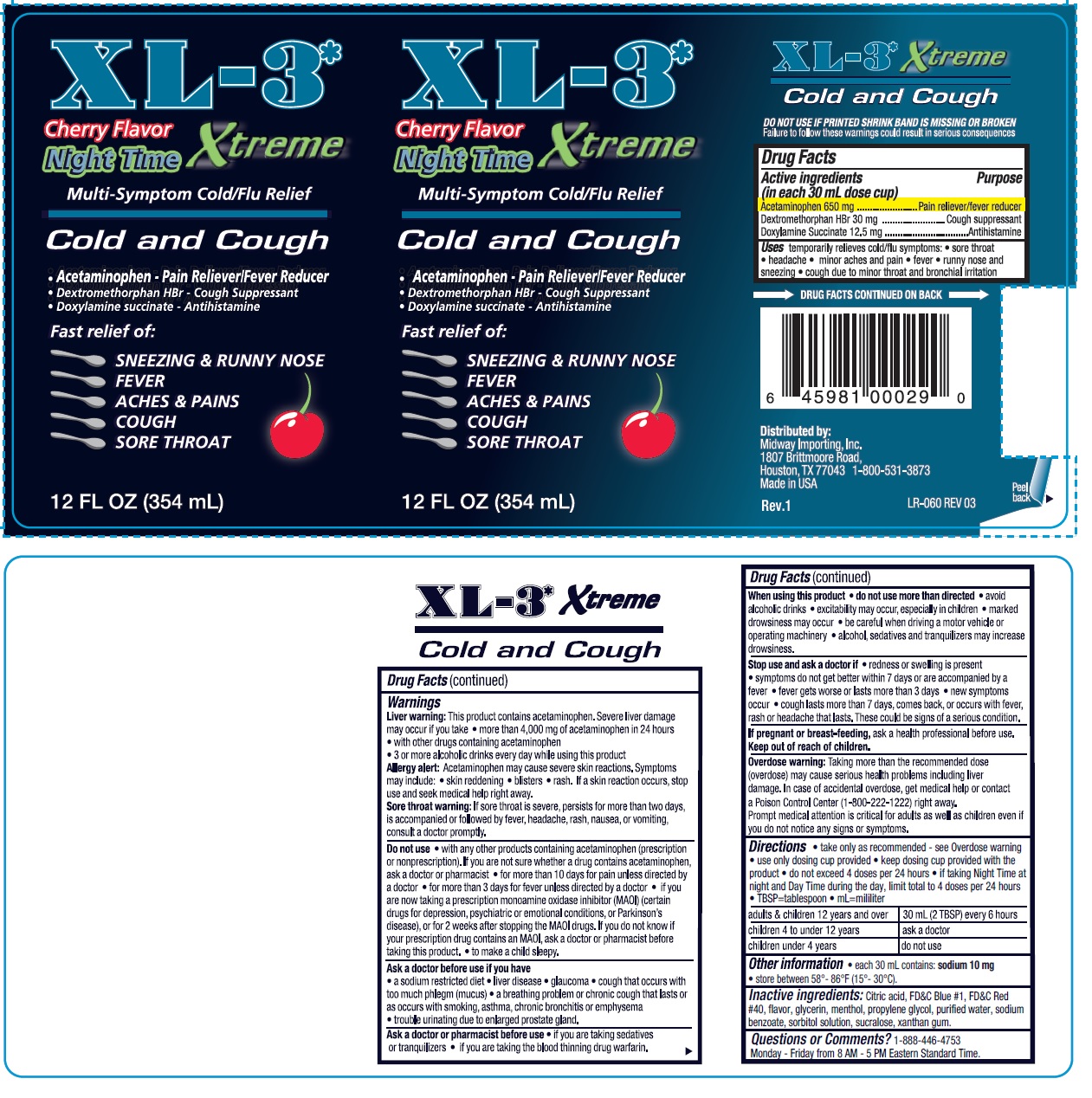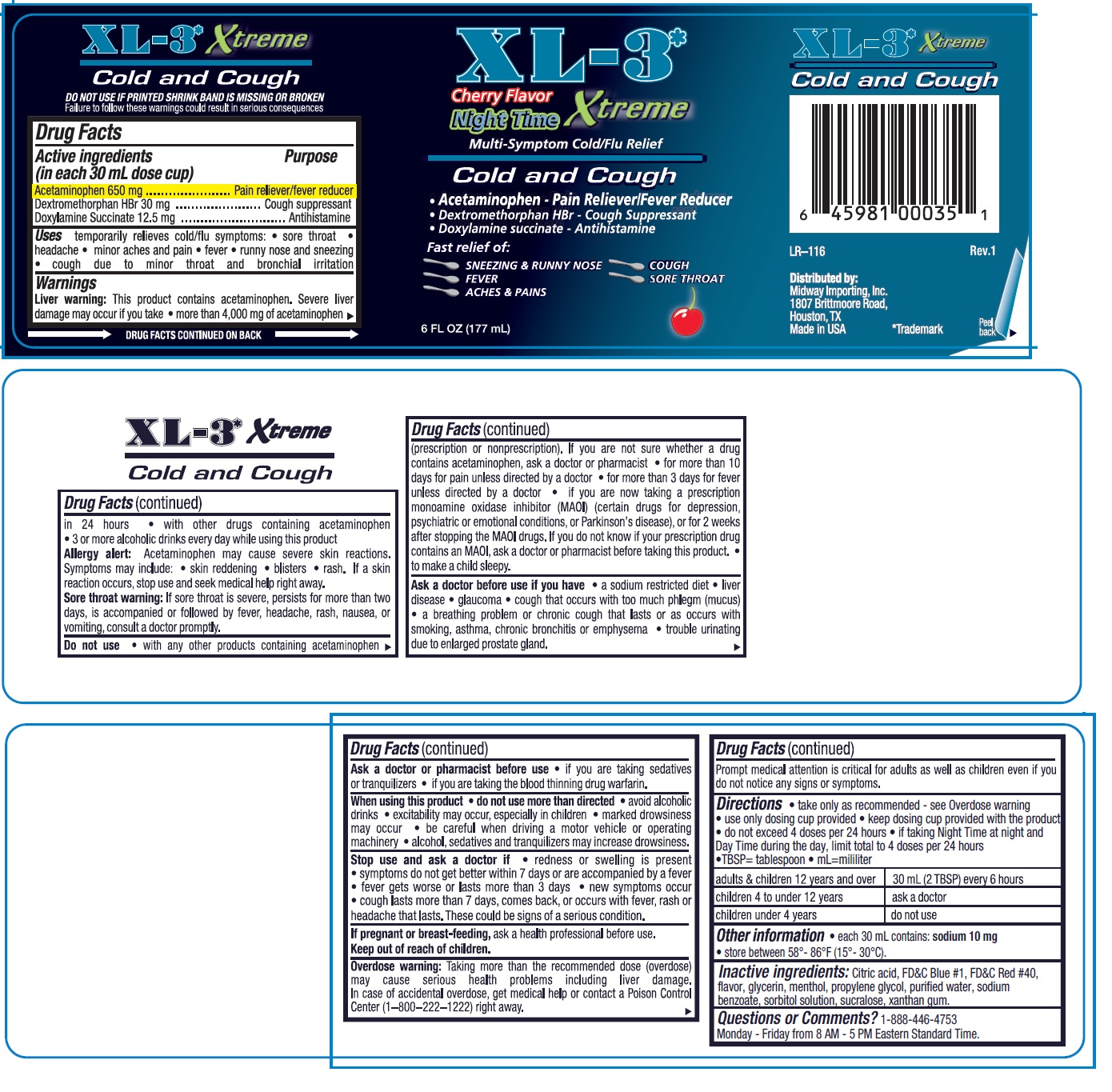 DRUG LABEL: XL-3 Night Time
NDC: 84379-444 | Form: LIQUID
Manufacturer: Rnv LLC
Category: otc | Type: HUMAN OTC DRUG LABEL
Date: 20260127

ACTIVE INGREDIENTS: DOXYLAMINE SUCCINATE 12.5 mg/30 mL; ACETAMINOPHEN 650 mg/30 mL; DEXTROMETHORPHAN HYDROBROMIDE 30 mg/30 mL
INACTIVE INGREDIENTS: PROPYLENE GLYCOL; FD&C RED NO. 40; SODIUM BENZOATE; SUCRALOSE; XANTHAN GUM; CITRIC ACID; FD&C BLUE NO. 1; SORBITOL SOLUTION; MENTHOL; GLYCERIN; WATER

XL-3 Night Time

Active ingredientes

(in each 30mL dose cup)

Acetaminophen 650 mg

Dextromethorphan HBr 30 mg

Doxylamine Succinate 12.5 mg

PURPOSE

Pain reliever/fever reducer

Cough Suppressant

Antihistamine

Uses

temporarily relieves cold/flu symptoms:

- sore throat
- headache
- minor aches and pain
- fever
- runny nose and sneezing
- cough due to minor throat and bronchial irritation

Warnings

Liver warning: This product contains acetaminophen. Sever liver damage may occur if you take

- more than 4,000 mg of acetaminophen in 24 hours
- with other drugs containing acetaminophen
- 3 or more alcoholic drinks every day while using this product

Allergy alert: Acetaminophen may cause sever skin reactions. Symptoms may include:

- skin reddening
- blisters
- rash

If skin reaction occurs, stop use and seek medical help right away.

Sore throat warning: If sore throat is sever, persist for more than two days, is accompanied or followed by fever, headache, rash, nausea, or vomiting, consult a doctor promptly

Do not use

with any other products containing acetaminophen (prescription or nonprescription). If you are not sure whether a drug contains acetaminophen, ask a doctor or pharmacist

- for more than 10 days for pain unless directed by a doctor
- for more than 3 days for fever unless directed by a doctor
- if you are now taking a prescription monoamine oxidase inhibitor (MAOI) (certain drugs for depression, psychiatric or emotional conditions, or Parkinson's diseas), or for 2 weeks after stopping the MAOI drugs. If you do not know if your prescription drug contains an MAOI, ask a doctor or pharmacist before taking this product.
- to make a child sleepy

Ask a doctor before use if you have

- a sodium restricted diet
- liver disease
- glaucoma
- cough that occurs with too much phlegm (mucus)
- a breathing problem or chronic cough that lasts or as occurs wtih smoking, asthma, chronic bronchitis or emphysema
- trouble urinating due to enlarged prostate gland

Ask a doctor or pharmacist before use

- if you are taking sedatives or tranquilizers
- if you are taking the blood thinning drug warfarin.

When using this product

- do not use more than directed
- avoid alcoholic drinks
- excitability may occur, especially in children
- marked drowsiness may occur
- be careful when driving a motor vehicle or operating machinery
- alcohol, sedatives and tranquilizers may increase drowsiness.

Stop use and ask a doctor if

- redness or swelling is present
- symptoms do not get better within 7 days or are accompanied by a fever
- fever gets worse or lasts more than 3 days
- new symptoms occur
- cough lasts more than 7 days, comes back, or occurs wih fever, rash or headache that lasts. These could be signs of a serious condition.

PREGNANCY OR BREAST FEEDING

If pregnant or breast-feeding, ask a health professional before use.

Keep out of reach of children.

OVERDOSAGE

Overdose warning: Taking more than the recommended dose (overdose) may cause serious health problems including liver damage. In case of accidental overdose, get medical help or contact a Poison Control Center (1-800-222-1222) right away. Prompt medical attention is critical for adults as well as children even if you do not notice any signs or symptoms.

DOSAGE AND ADMINISTRATION

- take only as recommended- see Overdose warning
- use only dosing cup provided
- keep dosing cup provided with the product
- do not exceed 4 doses per 24 hours
- if taking Day Time during the day and Night Time at night, limit the total to 4 doses per 24 hours
- TBSP=tablespoon
- mL=mililiter

adults & children 12 years and over | 30 mL (2 TBSP) every 6 hours
children 4 to under 12 years | ask a doctor
children under 4 years | do not use

Other information

- each 30 mL contains: sodium 10 mg
- store between 58° - 86°F (15°-30° degrees C)

INACTIVE INGREDIENT

Inactive ingredients: Citric acid, FD&C Blue #1, FD&C Red #40, flavor, glycerin, menthol, propylene glycol, purified water, sodium benzoate, sorbitol solution, sucralose, xanthan gum.

Questions or Comments? 1-888-446-4753

Monday - Friday from 8 AM - 5 PM Eastern Standard Time